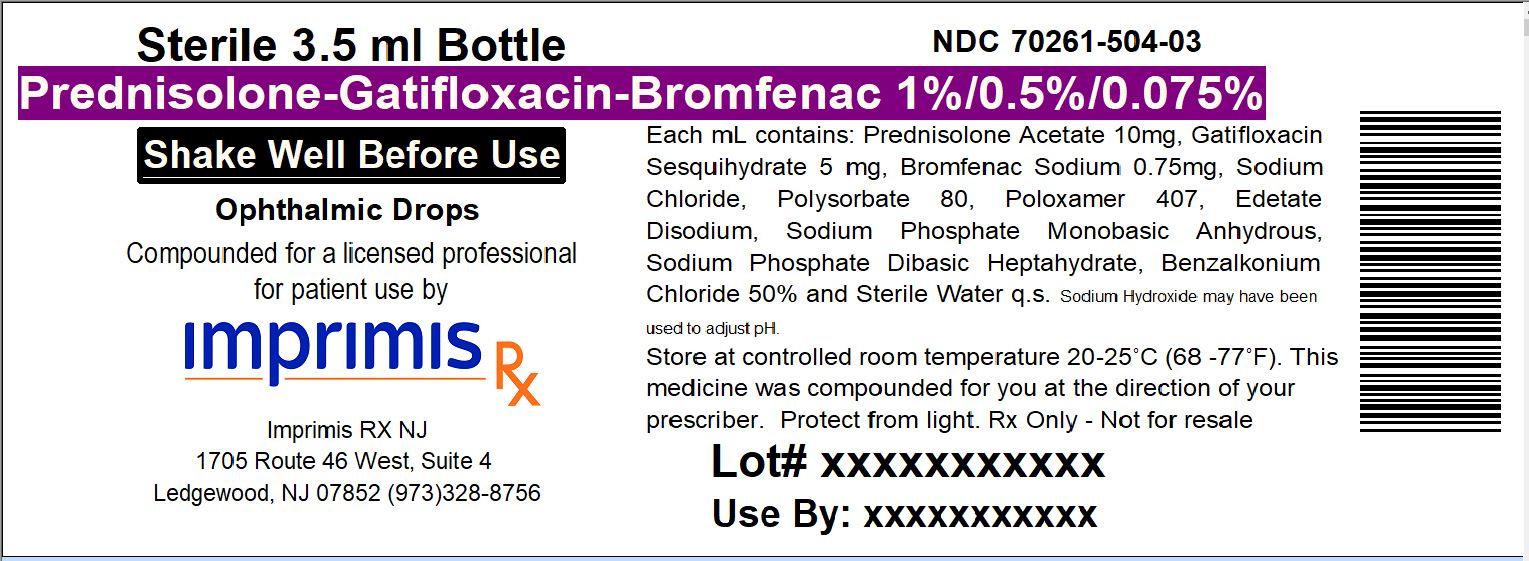 DRUG LABEL: Pred-Gati-Brom
NDC: 70261-504 | Form: SUSPENSION/ DROPS
Manufacturer: ImprimisRx NJ
Category: prescription | Type: HUMAN PRESCRIPTION DRUG LABEL
Date: 20180222

ACTIVE INGREDIENTS: GATIFLOXACIN HEMIHYDRATE 5 mg/1 mL; BROMFENAC 0.75 mg/1 mL; PREDNISOLONE ACETATE 10 mg/1 mL

STORAGE AND HANDLING

Store at 20° to 25° C (68° to 77° F)